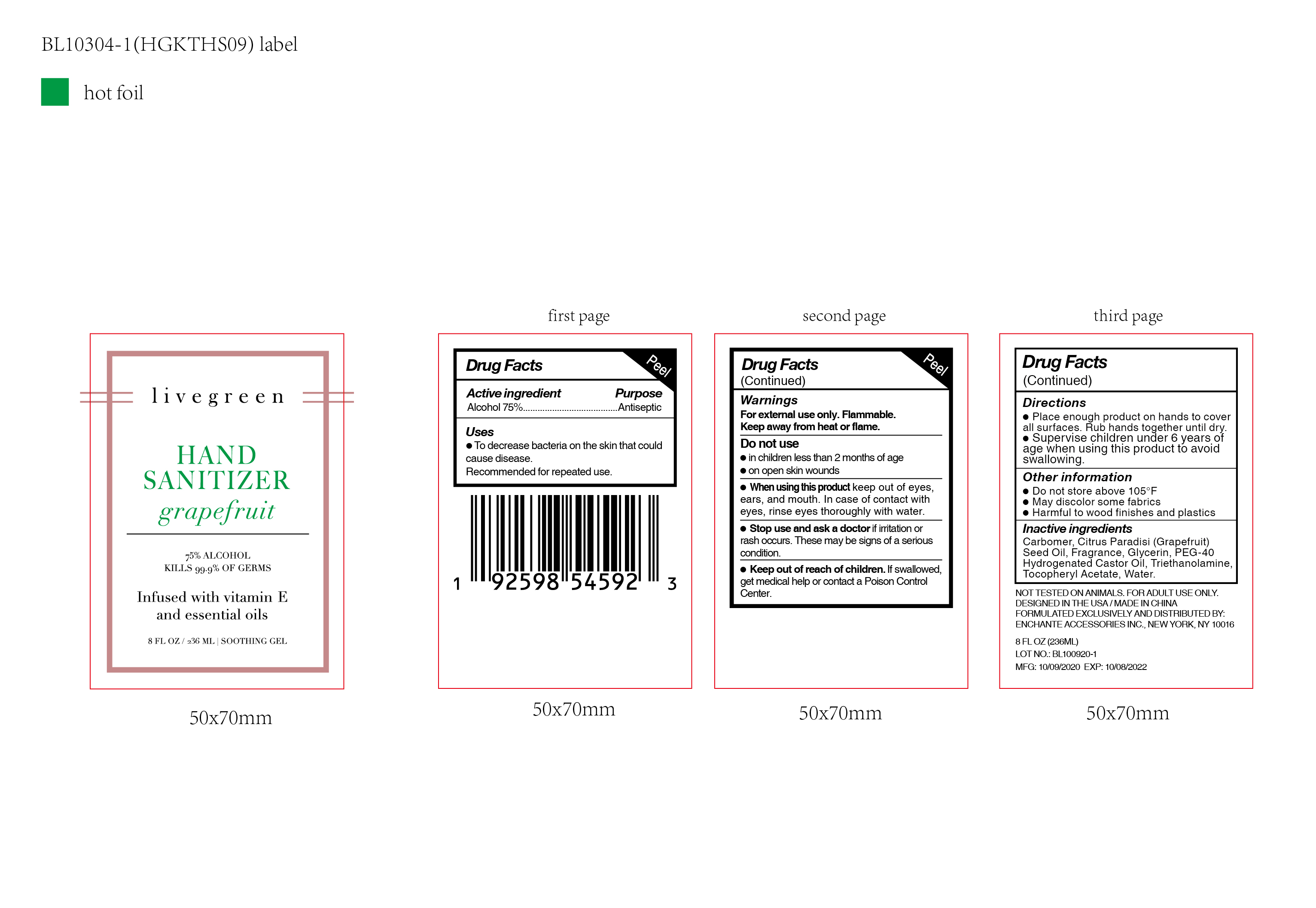 DRUG LABEL: livegreen HAND SANITIZER grapefruit infused with vitamin E and essential oils
NDC: 50563-341 | Form: SOLUTION
Manufacturer: ENCHANTE ACCESSORIES INC.
Category: otc | Type: HUMAN OTC DRUG LABEL
Date: 20201013

ACTIVE INGREDIENTS: ALCOHOL 75 mL/100 mL
INACTIVE INGREDIENTS: TROLAMINE; WATER; GLYCERIN; CARBOMER 940; POLYOXYL 40 HYDROGENATED CASTOR OIL; .ALPHA.-TOCOPHEROL ACETATE; GRAPEFRUIT SEED OIL

50563-341/ HGKTHS09

Active Ingredient

Alcohol: 75% (v/v)

Purpose

Antiseptic

Use

■ To decrease bacteria on the skin that could cause disease
■Recommended for repeated use

WARNINGS

For external use only

Flammable. Keep away from heat or flame

Do not use

in children less than two months of age

on open skin wounds

When using this product, keep out of eyes, ears, and mouth
In case of contact with eyes, rinse eyes thoroughly with water

Stop use and ask a doctor if irritation or rash occurs. These may be signs of a serious condition

Keep out of reach of children. If swallowed, get medical help or contact a poison control center

Directions

Place enough product on hands to cover all surfaces. Rub hands together untill dry.

Supervise children under six years of age when using this product to avoid swallowing

Other information

Do not store above 105F

May discolor some fabrics

Harmful to wood finishes and plastics

Inactive ingredients

Carbomer, Citrus Paradisi (Grapefruit) Seed Oil, Fragrance, Glycerin, PEG-40 Hydrogenated Castor Oil, Triehtanolamine, Tocopheryl Acetate, Water